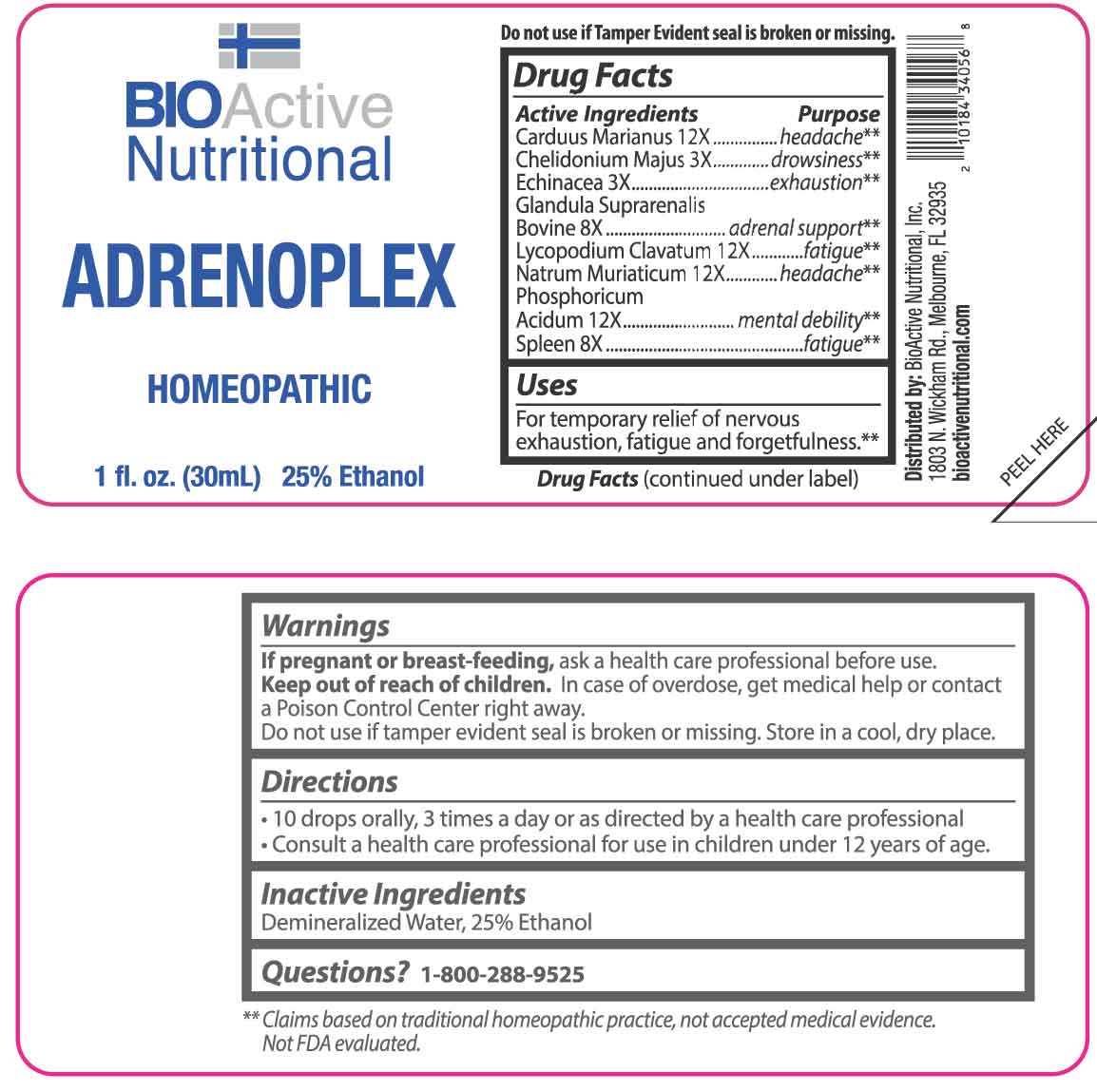 DRUG LABEL: ADRENOPLEX
NDC: 43857-0331 | Form: LIQUID
Manufacturer: BioActive Nutritional, Inc.
Category: homeopathic | Type: HUMAN OTC DRUG LABEL
Date: 20251218

ACTIVE INGREDIENTS: CHELIDONIUM MAJUS WHOLE 3 [hp_X]/1 mL; ECHINACEA ANGUSTIFOLIA WHOLE 3 [hp_X]/1 mL; BOS TAURUS ADRENAL GLAND 8 [hp_X]/1 mL; SUS SCROFA SPLEEN 8 [hp_X]/1 mL; MILK THISTLE 12 [hp_X]/1 mL; LYCOPODIUM CLAVATUM SPORE 12 [hp_X]/1 mL; SODIUM CHLORIDE 12 [hp_X]/1 mL; PHOSPHORIC ACID 12 [hp_X]/1 mL
INACTIVE INGREDIENTS: WATER; ALCOHOL

DRUG FACTS:

ACTIVE INGREDIENTS:

Carduus Marianus 12X, Chelidonium Majus 3X, Echinacea 3X, Glandula Suprarenalis Bovine 8X, Lycopodium Clavatum 12X, Natrum Muriaticum 12X, Phosphoricum Acidum 12X, Spleen 8X.

PURPOSE:

Carduus Marianus - headache,** Chelidonium Majus - drowsiness,** Echinacea - exhaustion,** Glandula Suprarenalis Bovine – adrenal support,** Lycopodium Clavatum - fatigue,** Natrum Muriaticum - headache,** Phosphoricum Acidum – mental debility,** Spleen – fatigue**

**Claims based on traditional homeopathic practice, not accepted medical evidence. Not FDA evaluated.

USES:

For temporary relief of nervous exhaustion, fatigue and forgetfulness.**

**Claims based on traditional homeopathic practice, not accepted medical evidence. Not FDA evaluated.

WARNINGS:

If pregnant or breast-feeding, ask a health care professional before use.

Keep out of reach of children. In case of overdose, get medical help or contact a Poison Control Center right away.

Do not use if tamper evident seal is broken or missing.

Store in a cool, dry place.

KEEP OUT OF REACH OF CHILDREN

In case of overdose, get medical help or contact a Poison Control Center right away.

DIRECTIONS:

• 10 drops orally, 3 times a day or as directed by a health care professional.

• Consult a health care professional for use in children under 12 years of age.

INACTIVE INGREDIENTS

Demineralized Water, 25% Ethanol

QUESTIONS:

Distributed by:
BioActive Nutritional, Inc.
1803 N. Wickham Rd.
Melbourne, FL 32935
bioactivenutritional.com

1-800-288-9525

PACKAGE LABEL DISPLAY:

BIOActive Nutritional

ADRENOPLEX

HOMEOPATHIC

1 fl. oz. (30 mL)